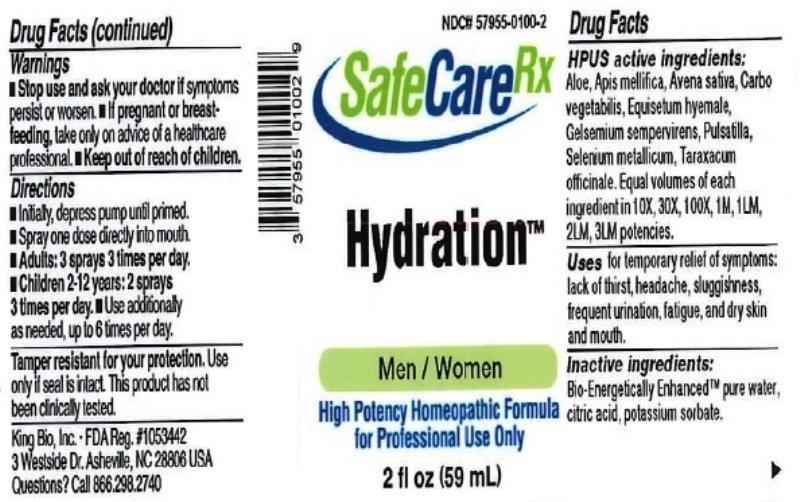 DRUG LABEL: Hydration
NDC: 57955-0100 | Form: LIQUID
Manufacturer: King Bio Inc.
Category: homeopathic | Type: HUMAN OTC DRUG LABEL
Date: 20170116

ACTIVE INGREDIENTS: ALOE 10 [hp_X]/59 mL; APIS MELLIFERA 10 [hp_X]/59 mL; AVENA SATIVA FLOWERING TOP 10 [hp_X]/59 mL; ACTIVATED CHARCOAL 10 [hp_X]/59 mL; EQUISETUM HYEMALE 10 [hp_X]/59 mL; GELSEMIUM SEMPERVIRENS ROOT 10 [hp_X]/59 mL; PULSATILLA VULGARIS 10 [hp_X]/59 mL; SELENIUM 10 [hp_X]/59 mL; TARAXACUM OFFICINALE 10 [hp_X]/59 mL
INACTIVE INGREDIENTS: WATER; ANHYDROUS CITRIC ACID; POTASSIUM SORBATE

Hydration

ACTIVE INGREDIENT

HPUS active ingredients: Aloe socotrina, Apis mellifica, Avena sativa, Carbo vegetabilis, Equisetum hyemale, Gelsemium sempervirens, Pulsatilla, Selenium metallicum, Taraxacum officinale. Equal volumes of each ingredient in 10X, 30X, 100X, 1M, 1LM, 2LM, 3LM potencies.

PURPOSE

Uses for temporary relief of symptoms: lack of thirst, headache, sluggishness, frequent urination, fatigue, and dry skin and mouth.

Inactive Ingredients:

Bio-Energetically Enhanced™ pure water, citric acid and potassium sorbate.

Warning

- Stop use and ask a doctor if symptoms persist or worsen.
- If pregnant or breast-feeding, take only on advice of a healthcare professional.

- Keep out of reach of children.

Directions

- Initially, depress pump until primed.
- Spray one dose directly into mouth.
- Adults: 3 sprays 3 times per day.
- Children 2-12 years: 2 sprays 3 times per day.
- Use additionally as needed, up to 6 times per day.

OTHER SAFETY INFORMATION

Tamper resistant for your protection. Use only if safety seal is intact. This product had not been clinically tested.

INDICATIONS AND USAGE

Uses for temporary relief of symptoms:

- lack of thirst
- headache
- sluggishness
- frequent urination
- fatigue and dry skin and mouth